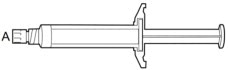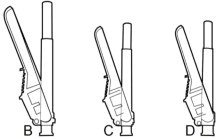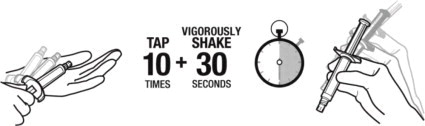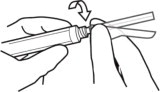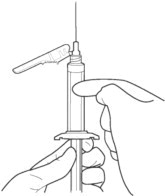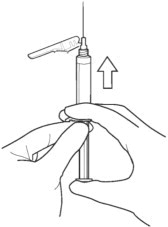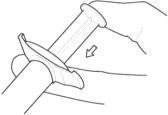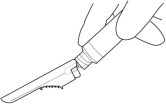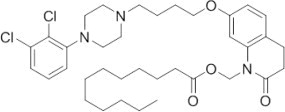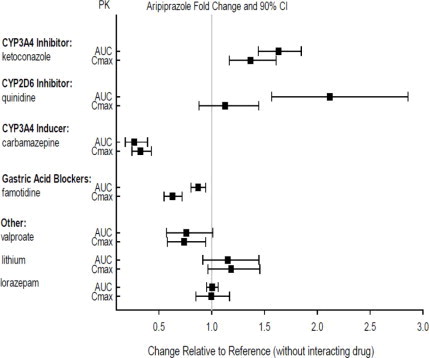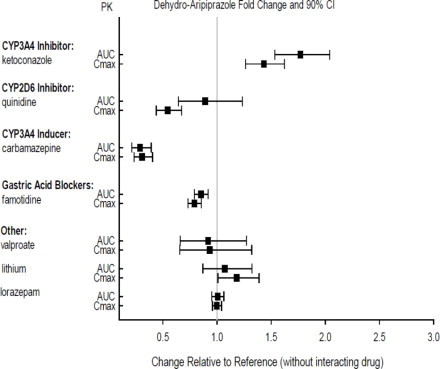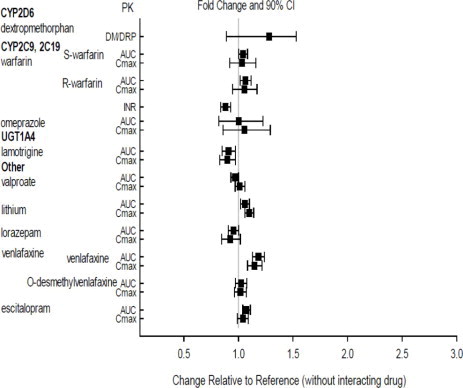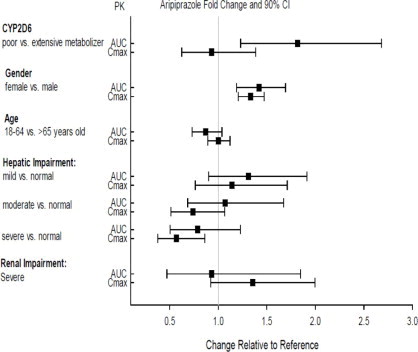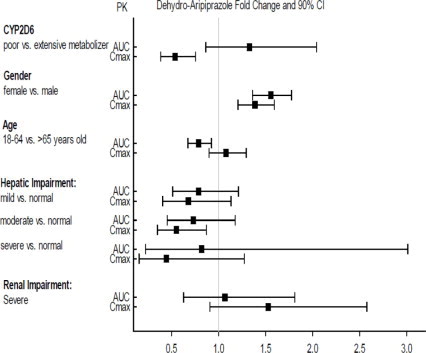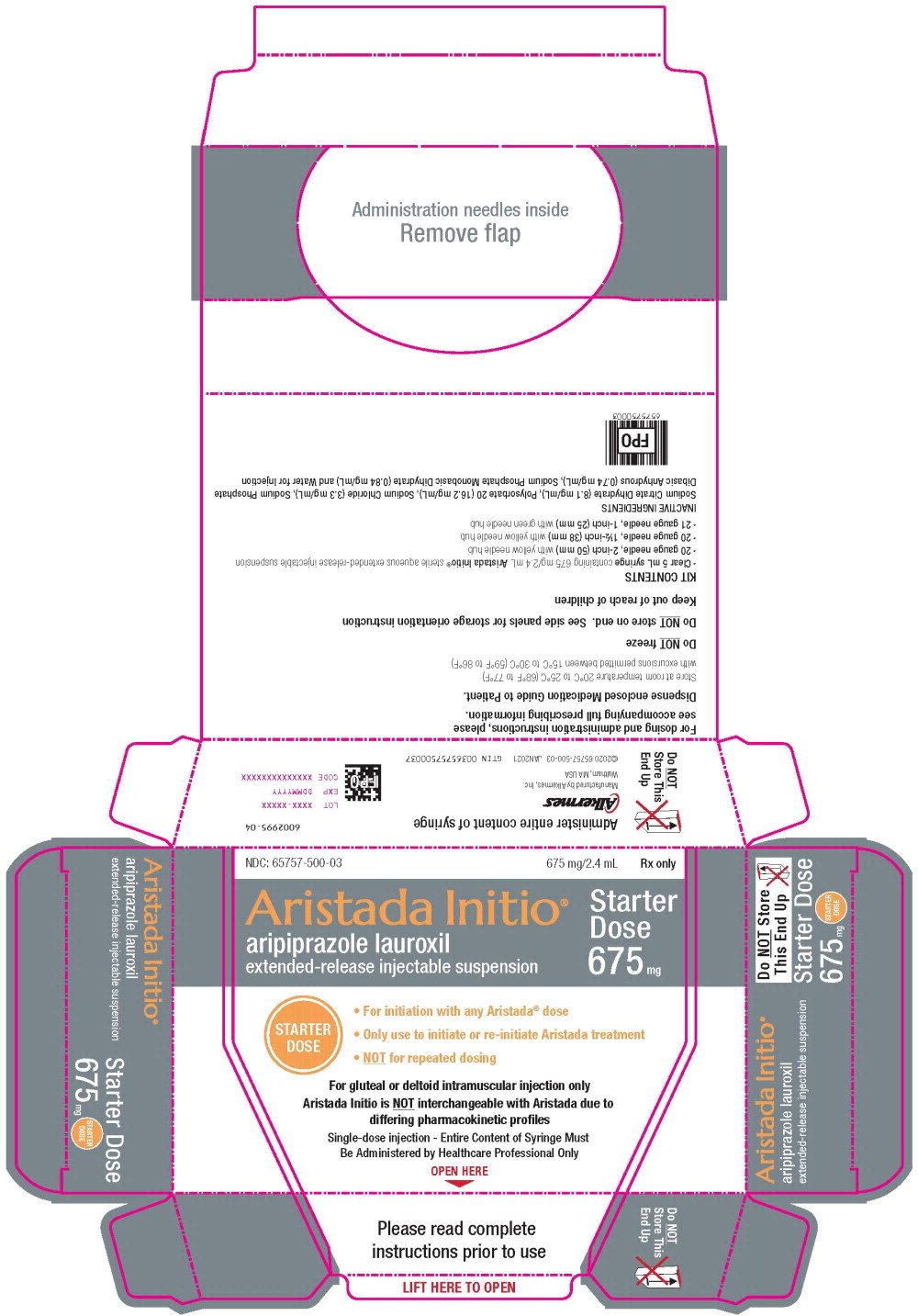 DRUG LABEL: ARISTADA INITIO
NDC: 65757-500 | Form: INJECTION, SUSPENSION, EXTENDED RELEASE
Manufacturer: Alkermes, Inc.
Category: prescription | Type: HUMAN PRESCRIPTION DRUG LABEL
Date: 20250128

ACTIVE INGREDIENTS: aripiprazole lauroxil 675 mg/2.4 mL
INACTIVE INGREDIENTS: Polysorbate 20; Sodium Chloride; Trisodium Citrate Dihydrate; Sodium Phosphate, Dibasic, Anhydrous; Sodium Phosphate, Monobasic, Dihydrate; Water

HIGHLIGHTS OF PRESCRIBING INFORMATION

These highlights do not include all the information needed to use ARISTADA INITIO® safely and effectively. See full prescribing information for ARISTADA INITIO®.
ARISTADA INITIO® (aripiprazole lauroxil) extended-release injectable suspension, for intramuscular use
Initial U.S. Approval: 2015

WARNING: INCREASED MORTALITY IN ELDERLY PATIENTS WITH DEMENTIA-RELATED PSYCHOSIS

See full prescribing information for complete boxed warning.

- Elderly patients with dementia-related psychosis treated with antipsychotic drugs are at an increased risk of death. (5.1)
- ARISTADA INITIO is not approved for the treatment of patients with dementia-related psychosis. (5.1)

1 INDICATIONS AND USAGE

ARISTADA INITIO, in combination with oral aripiprazole, is indicated for the initiation of ARISTADA® when used for the treatment of schizophrenia in adults (1).

2 DOSAGE AND ADMINISTRATION

- Administer one 675 mg injection of ARISTADA INITIO and one 30 mg dose of oral aripiprazole in conjunction with the first ARISTADA injection (2.1).
- ARISTADA INITIO is only to be used as a single dose and is not for repeated dosing (2.1).
- Administer ARISTADA INITIO by intramuscular injection in either the deltoid or gluteal muscle by a healthcare professional (2.1).
- For patients naïve to aripiprazole, establish tolerability with oral aripiprazole prior to initiating treatment with ARISTADA INITIO (2.1).
- See Dosage and Administration for detailed preparation and administration instructions (2.4).
- Avoid use in known CYP2D6 poor metabolizers (2.3, 7.1).
- Avoid use with strong CYP2D6 or CYP 3A4 inhibitors and strong CYP3A4 inducers (2.3, 7.1).
- ARISTADA INITIO is not interchangeable with ARISTADA (2.1, 5.3).

3 DOSAGE FORMS AND STRENGTHS

Extended-release injectable suspension: 675 mg single-dose pre-filled syringe (3).

4 CONTRAINDICATIONS

Known hypersensitivity to aripiprazole (4).

5 WARNINGS AND PRECAUTIONS

- Cerebrovascular Adverse Reactions in Elderly Patients with Dementia-Related Psychosis: Increased incidence of cerebrovascular adverse reactions (e.g., stroke, transient ischemia attack, including fatalities) (5.2).
- Potential for Dosing and Medication Errors: Substitution and dispensing errors between ARISTADA INITIO and ARISTADA could occur. Do not substitute ARISTADA INITIO for ARISTADA (5.3).
- Neuroleptic Malignant Syndrome: Manage with immediate discontinuation and close monitoring (5.4).
- Tardive Dyskinesia: Discontinue if clinically appropriate (5.5).
- Metabolic Changes: Monitor for hyperglycemia, dyslipidemia, and weight gain (5.6).
- Pathological Gambling and Other Compulsive Behaviors: Consider discontinuation (5.7).
- Orthostatic Hypotension: Monitor heart rate and blood pressure and warn patients with known cardiovascular or cerebrovascular disease, and risk of dehydration or syncope (5.8).
- Leukopenia, Neutropenia, and Agranulocytosis: Perform complete blood counts in patients with a history of a clinically significant low white blood cell (WBC) count. Consider discontinuation if clinically significant decline in WBC in the absence of other causative factors (5.10).
- Seizures: Use cautiously in patients with a history of seizures or with conditions that lower the seizure threshold (5.11).
- Potential for Cognitive and Motor Impairment: Use caution when operating machinery (5.12).

6 ADVERSE REACTIONS

Most commonly observed adverse reaction (incidence ≥5% and at least twice that for placebo) was akathisia (6.1).

To report SUSPECTED ADVERSE REACTIONS, contact Alkermes, Inc. at 1-866-274-7823 or FDA at 1-800-FDA-1088 or
WWW.FDA.GOV/MEDWATCH.

8 USE IN SPECIFIC POPULATIONS

- Pregnancy: May cause extrapyramidal and/or withdrawal symptoms in neonates in women exposed during the third trimester of pregnancy (8.1).
- Lactation: Monitor the breastfed infant for dehydration and lack of appropriate weight gain (8.2).

FULL PRESCRIBING INFORMATION

WARNING: INCREASED MORTALITY IN ELDERLY PATIENTS WITH DEMENTIA-RELATED PSYCHOSIS

Elderly patients with dementia-related psychosis treated with antipsychotic drugs are at an increased risk of death. ARISTADA INITIO is not approved for the treatment of patients with dementia-related psychosis [see Warnings and Precautions (5.1)].

1 INDICATIONS AND USAGE

ARISTADA INITIO, in combination with oral aripiprazole, is indicated for the initiation of ARISTADA when used for the treatment of schizophrenia in adults.

2 DOSAGE AND ADMINISTRATION

2.1 Recommended Dosage

ARISTADA INITIO is only to be used as a single dose to initiate ARISTADA treatment or as a single dose to re-initiate ARISTADA treatment following a missed dose of ARISTADA. ARISTADA INITIO is not for repeated dosing.

ARISTADA INITIO is not interchangeable with ARISTADA due to differing pharmacokinetic profiles [see Warnings and Precautions (5.3)].

ARISTADA INITIO is to be administered as an intramuscular injection by a healthcare professional.

For patients who have never taken aripiprazole, establish tolerability with oral aripiprazole prior to initiating treatment with ARISTADA INITIO. Due to the half-life of oral aripiprazole, it may take up to 2 weeks to fully assess tolerability. Refer to the prescribing information of oral aripiprazole for the recommended dosage and administration of the oral formulation.

After establishing tolerability with oral aripiprazole, administer the first ARISTADA intramuscular injection (441 mg, 662 mg, 882 mg, or 1064 mg) in conjunction with both:

- One 675 mg injection of ARISTADA INITIO in the deltoid or gluteal muscle (which corresponds to 459 mg of aripiprazole) [see Clinical Pharmacology (12.3)]; and
- One 30 mg dose of oral aripiprazole.

The first ARISTADA injection may be administered on the same day as ARISTADA INITIO or up to 10 days thereafter. See the ARISTADA prescribing information for additional information regarding dosage and administration of ARISTADA.

Avoid injecting both ARISTADA INITIO and ARISTADA concomitantly into the same deltoid or gluteal muscle.

2.2 Missed Doses of ARISTADA

ARISTADA INITIO may be used to re-initiate treatment with ARISTADA following a missed dose of ARISTADA. When a dose of ARISTADA is missed, administer the next injection of ARISTADA as soon as possible. Depending on the time elapsed since the last ARISTADA injection, supplement the next ARISTADA injection as recommended in Table 1 below.

Table 1: Recommendation for Concomitant Supplementation Following Missed Doses of ARISTADA
Dose of Patient's Last ARISTADA Injection | Length of Time Since Last Injection
441 mg | ≤ 6 weeks | > 6 and ≤ 7 weeks | > 7 weeks
662 mg | ≤ 8 weeks | > 8 and ≤ 12 weeks | > 12 weeks
882 mg | ≤ 8 weeks | > 8 and ≤ 12 weeks | > 12 weeks
1064 mg | ≤ 10 weeks | > 10 and ≤ 12 weeks | > 12 weeks
Dosage and Administration for Re-initiation of ARISTADA | No Supplementation Required | Supplement with a Single Dose of ARISTADA INITIO | Re-initiate with a Single Dose of ARISTADA INITIO and a Single Dose of Oral Aripiprazole 30 mg

2.3 Dose Adjustments for CYP450 Considerations

ARISTADA INITIO is only available at a single strength as a single-dose pre-filled syringe, so dosage adjustments are not possible. Therefore, avoid use in patients who are known CYP2D6 poor metabolizers or taking strong CYP3A4 inhibitors, strong CYP2D6 inhibitors, or strong CYP3A4 inducers.

2.4 Important Administration Instructions

The kit contains a syringe containing ARISTADA INITIO sterile aqueous extended-release injectable suspension and 3 safety needles (a 2-inch 20 gauge needle with yellow needle hub, a 1 ½-inch 20 gauge needle with yellow needle hub, and a 1-inch 21 gauge needle with green needle hub) for intramuscular injection. Store all materials at room temperature.

A | 5 mL syringe containing 675 mg/2.4 mL ARISTADA INITIO sterile aqueous extended-release injectable suspension
B | 20 gauge needle, 2-inch with yellow needle hub
C | 20 gauge needle, 1½-inch with yellow needle hub
D | 21 gauge needle, 1-inch with green needle hub

1. TAP and vigorously SHAKE the syringe.

1a. Tap the syringe at least 10 times to dislodge any material which may have settled.

1b. Shake the syringe vigorously for a minimum of 30 seconds to ensure a uniform suspension. If the syringe is not used within 15 minutes, shake again for 30 seconds.

2. SELECT the injection needle.

2a. Select injection site.

2b. Select needle length based on injection site. For patients with a larger amount of subcutaneous tissue overlaying the injection site muscle, use the longer of the needles provided.

Table 2: ARISTADA INITIO Injection Site and Associated Needle Length
Injection Site | Needle Length
675 mg dose
Deltoid | 21 gauge, 1-inch or 20 gauge, 1½-inch
Gluteal | 20 gauge, 1½-inch or 20 gauge, 2-inch

3. ATTACH the injection needle.

Attach the appropriate needle securely with a clockwise twisting motion. Do NOT overtighten. Overtightening could lead to needle hub cracking.

4. PRIME the syringe to remove air.

4a. Bring the syringe into upright position and tap the syringe to bring air to the top.

4b. Depress the plunger rod to remove air until a few drops are released. It is normal to see small air bubbles remaining in the syringe.

5. Inject in a RAPID and CONTINUOUS manner. Product requires a RAPID injection. Do not hesitate. Administer the entire content intramuscularly. Do not inject by any other route.

6. DISPOSE of the needle. Cover the needle by pressing the safety device. Dispose of used and unused items in a proper waste container.

3 DOSAGE FORMS AND STRENGTHS

ARISTADA INITIO is a white to off-white aqueous extended-release injectable suspension provided in a single-dose pre-filled syringe (see Table 3).

Table 3: Presentation of ARISTADA INITIO
Dose Strength | Volume | Inject Intramuscularly | Color Label
675 mg | 2.4 mL | Deltoid or Gluteal Muscle | Gray

4 CONTRAINDICATIONS

ARISTADA INITIO is contraindicated in patients with a known hypersensitivity reaction to aripiprazole. Hypersensitivity reactions have ranged from pruritus/urticaria to anaphylaxis [see Adverse Reactions (6)].

5 WARNINGS AND PRECAUTIONS

5.1 Increased Mortality in Elderly Patients with Dementia-related Psychosis

Elderly patients with dementia-related psychosis treated with antipsychotic drugs are at an increased risk of death. Analyses of 17 placebo-controlled trials (modal duration of 10 weeks), largely in patients taking atypical antipsychotic drugs, revealed a risk of death in drug-treated patients of between 1.6 to 1.7 times the risk of death in placebo-treated patients. Over the course of a typical 10-week controlled trial, the rate of death in drug-treated patients was about 4.5%, compared to a rate of about 2.6% in the placebo group.

Although the causes of death were varied, most of the deaths appeared to be either cardiovascular (e.g., heart failure, sudden death) or infectious (e.g., pneumonia) in nature. Observational studies suggest that, similar to atypical antipsychotic drugs, treatment with conventional antipsychotic drugs may increase mortality. The extent to which the findings of increased mortality in observational studies may be attributed to the antipsychotic drug as opposed to some characteristic(s) of the patients is not clear. ARISTADA INITIO is not approved for the treatment of patients with dementia-related psychosis [see Boxed Warning, Warnings and Precautions (5.2)].

5.2 Cerebrovascular Adverse Reactions, Including Stroke

In placebo-controlled trials with risperidone, aripiprazole, and olanzapine in elderly patients with dementia, there was a higher incidence of cerebrovascular adverse reactions (cerebrovascular accidents and transient ischemic attacks) including fatalities compared to placebo-treated patients. ARISTADA INITIO is not approved for the treatment of patients with dementia-related psychosis [see Boxed Warning, Warnings and Precautions (5.1)].

5.3 Potential for Dosing and Medication Errors

Medication errors, including substitution and dispensing errors, between ARISTADA INITIO and ARISTADA could occur. ARISTADA INITIO is intended for single administration only. Do not substitute ARISTADA INITIO for ARISTADA because of differing pharmacokinetic profiles [see Dosage and Administration (2.1)].

5.4 Neuroleptic Malignant Syndrome

A potentially fatal symptom complex sometimes referred to as Neuroleptic Malignant Syndrome (NMS) may occur in association with antipsychotic drugs, including ARISTADA INITIO. Clinical manifestations of NMS are hyperpyrexia, muscle rigidity, altered mental status, and evidence of autonomic instability (irregular pulse or blood pressure, tachycardia, diaphoresis, and cardiac dysrhythmia). Additional signs may include elevated creatine phosphokinase, myoglobinuria (rhabdomyolysis), and acute renal failure.

The diagnostic evaluation of patients with this syndrome is complicated. In arriving at a diagnosis, it is important to identify cases in which the clinical presentation includes both serious medical illness (e.g., pneumonia, systemic infection, etc.) and untreated or inadequately treated extrapyramidal signs and symptoms (EPS). Other important considerations in the differential diagnosis include central anticholinergic toxicity, heat stroke, drug fever, and primary central nervous system pathology.

The management of NMS should include: (1) immediate discontinuation of antipsychotic drugs and other drugs not essential to concurrent therapy; (2) intensive symptomatic treatment and medical monitoring; and (3) treatment of any concomitant serious medical problems for which specific treatments are available. There is no general agreement about specific pharmacological treatment regimens for uncomplicated NMS.

If a patient appears to require antipsychotic drug treatment after recovery from NMS, reintroduction of drug therapy should be closely monitored, since recurrences of NMS have been reported.

5.5 Tardive Dyskinesia

A syndrome of potentially irreversible, involuntary, dyskinetic movements may develop in patients treated with antipsychotic drugs. Although the prevalence of the syndrome appears to be highest among the elderly, especially elderly women, it is impossible to predict which patients will develop the syndrome. Whether antipsychotic drug products differ in their potential to cause tardive dyskinesia is unknown.

The risk of developing tardive dyskinesia and the likelihood that it will become irreversible appear to increase as the duration of treatment and the total cumulative dose of antipsychotic drugs administered to the patient increase, but the syndrome can develop after relatively brief treatment periods at low doses, although this is uncommon.

Tardive dyskinesia may remit, partially or completely, if antipsychotic treatment is withdrawn. Antipsychotic treatment itself may suppress (or partially suppress) the signs and symptoms of the syndrome and may thus mask the underlying process. The effect of symptomatic suppression on the long-term course of the syndrome is unknown.

Given these considerations, antipsychotics should be prescribed in a manner that is most likely to minimize the occurrence of tardive dyskinesia. Chronic antipsychotic treatment should generally be reserved for patients who suffer from a chronic illness that is known to respond to antipsychotic drugs. In patients who do require chronic treatment, the smallest dose and the shortest duration of treatment producing a satisfactory clinical response should be sought. The need for continued treatment should be reassessed periodically.

If signs and symptoms of tardive dyskinesia appear in a patient treated with antipsychotics, consider discontinuation of the antipsychotic drug. However, some patients may require antipsychotic treatment despite the presence of the syndrome.

5.6 Metabolic Changes

Atypical antipsychotic drugs have been associated with metabolic changes that include hyperglycemia/diabetes mellitus, dyslipidemia, and weight gain. While all drugs in the class have been shown to produce some metabolic changes, each drug has its own specific risk profile.

Hyperglycemia/ Diabetes Mellitus

Hyperglycemia, in some cases extreme and associated with ketoacidosis or hyperosmolar coma or death, has been reported in patients treated with atypical antipsychotics. There have been reports of hyperglycemia in patients treated with oral aripiprazole. Assessment of the relationship between atypical antipsychotic use and glucose abnormalities is complicated by the possibility of an increased background risk of diabetes mellitus in patients with schizophrenia and the increasing incidence of diabetes mellitus in the general population. Given these confounders, the relationship between atypical antipsychotic use and hyperglycemia-related adverse events is not completely understood. However, epidemiological studies suggest an increased risk of hyperglycemia-related adverse reactions in patients treated with the atypical antipsychotics.

Patients with an established diagnosis of diabetes mellitus who are started on atypical antipsychotics should be monitored regularly for worsening of glucose control. Patients with risk factors for diabetes mellitus (e.g., obesity, family history of diabetes) who are starting treatment with atypical antipsychotics should undergo fasting blood glucose testing at the beginning of treatment and periodically during treatment. Any patient treated with atypical antipsychotics should be monitored for symptoms of hyperglycemia including polydipsia, polyuria, polyphagia, and weakness. Patients who develop symptoms of hyperglycemia during treatment with atypical antipsychotics should undergo fasting blood glucose testing. In some cases, hyperglycemia has resolved when the atypical antipsychotic was discontinued; however, some patients require continuation of anti-diabetic treatment despite discontinuation of the suspect drug.

Dyslipidemia

Undesirable alterations in lipids have been observed in patients treated with atypical antipsychotics.

Weight Gain

Weight gain has been observed with atypical antipsychotic use. Clinical monitoring of weight is recommended.

5.7 Pathological Gambling and Other Compulsive Behaviors

Post-marketing case reports suggest that patients can experience intense urges, particularly for gambling, and the inability to control these urges while taking aripiprazole. Other compulsive urges, reported less frequently include: sexual urges, shopping, eating or binge eating, and other impulsive or compulsive behaviors. Because patients may not recognize these behaviors as abnormal, it is important for prescribers to ask patients or their caregivers specifically about the development of new or intense gambling urges, compulsive sexual urges, compulsive shopping, binge or compulsive eating, or other urges while being treated with aripiprazole. It should be noted that impulse-control symptoms can be associated with the underlying disorder. In some cases, although not all, urges were reported to have stopped when the dose was reduced or the medication was discontinued. Compulsive behaviors may result in harm for the patient and others if not recognized. If compulsive urges develop, consider discontinuing aripiprazole.

5.8 Orthostatic Hypotension

Aripiprazole may cause orthostatic hypotension, perhaps due to its α1-adrenergic receptor antagonism. Associated adverse reactions related to orthostatic hypotension can include dizziness, lightheadedness and tachycardia. Generally, these risks are greatest at the beginning of treatment and during dose escalation. Patients at increased risk of these adverse reactions or at increased risk of developing complications from hypotension include those with dehydration, hypovolemia, treatment with antihypertensive medication, history of cardiovascular disease (e.g., heart failure, myocardial infarction, ischemia, or conduction abnormalities), history of cerebrovascular disease, as well as patients who are antipsychotic-naïve. In such patients, monitor orthostatic vital signs.

5.9 Falls

Antipsychotics including ARISTADA INITIO may cause somnolence, postural hypotension, or motor and sensory instability, which may lead to falls and, consequently, fractures or other injuries. For patients with diseases, conditions, or medications that could exacerbate these effects, complete fall risk assessments when initiating antipsychotic treatment and recurrently for those patients on long-term antipsychotic therapy.

5.10 Leukopenia, Neutropenia, and Agranulocytosis

In clinical trials and/or postmarketing experience, events of leukopenia and neutropenia have been reported temporally related to antipsychotic agents. Agranulocytosis has also been reported.

Possible risk factors for leukopenia/neutropenia include pre-existing low white blood cell count (WBC)/absolute neutrophil count (ANC) and history of drug-induced leukopenia/neutropenia. In patients with a history of a clinically significant low WBC/ANC or drug-induced leukopenia/neutropenia, perform a complete blood count (CBC) frequently during the first few months of therapy. In such patients, consider discontinuation of antipsychotics at the first sign of a clinical significant decline in WBC in the absence of other causative factors.

Monitor patients with clinically significant neutropenia for fever or other symptoms or signs of infection and treat promptly if such symptoms or signs occur. Discontinue antipsychotics in patients with severe neutropenia (absolute neutrophil count <1000/mm^3) and follow their WBC until recovery.

5.11 Seizures

As with other antipsychotic drugs, use ARISTADA INITIO cautiously in patients with a history of seizures or with conditions that lower the seizure threshold. Conditions that lower the seizure threshold may be more prevalent in a population of 65 years or older.

5.12 Potential for Cognitive and Motor Impairment

ARISTADA INITIO, like other antipsychotics, has the potential to impair judgment, thinking or motor skills. Patients should be cautioned about operating hazardous machinery, including automobiles, until they are reasonably certain that therapy with ARISTADA INITIO does not affect them adversely.

5.13 Body Temperature Regulation

Disruption of the body's ability to reduce core body temperature has been attributed to antipsychotic agents. Appropriate care is advised when prescribing ARISTADA INITIO for patients who will be experiencing conditions which may contribute to an elevation in core body temperature, (e.g., exercising strenuously, exposure to extreme heat, receiving concomitant medication with anticholinergic activity, or being subject to dehydration).

5.14 Dysphagia

Esophageal dysmotility and aspiration have been associated with antipsychotic drug use. ARISTADA INITIO and other antipsychotic drugs should be used cautiously in patients at risk for aspiration pneumonia.

6 ADVERSE REACTIONS

The following are discussed in more details in other sections of the labeling:

- Increased Mortality in Elderly Patients with Dementia-related Psychosis [see Boxed Warning, Warnings and Precautions (5.1)]
- Cerebrovascular Adverse Reactions, Including Stroke [see Boxed Warning, Warnings and Precautions (5.2)]
- Neuroleptic Malignant Syndrome [see Warnings and Precautions (5.4)]
- Tardive Dyskinesia [see Warnings and Precautions (5.5)]
- Metabolic Changes [see Warnings and Precautions (5.6)]
- Pathological Gambling and Other Compulsive Behaviors [see Warnings and Precautions (5.7)]
- Orthostatic Hypotension [see Warnings and Precautions (5.8)]
- Falls [see Warnings and Precautions (5.9)]
- Leukopenia, Neutropenia, and Agranulocytosis [see Warnings and Precautions (5.10)]
- Seizures [see Warnings and Precautions (5.11)]
- Potential for Cognitive and Motor Impairment [see Warnings and Precautions (5.12)]
- Body Temperature Regulation [see Warnings and Precautions (5.13)]
- Dysphagia [see Warnings and Precautions (5.14)]

6.1 Clinical Studies Experience

Because clinical trials are conducted under widely varying conditions, adverse reaction rates observed in the clinical trials of a drug cannot be directly compared to rates in the clinical trials of another drug and may not reflect the rates observed in practice.

The safety of ARISTADA INITIO, in combination with oral aripiprazole, for the initiation of ARISTADA when used for the treatment of schizophrenia in adults has been established and is based on clinical trials of ARISTADA (aripiprazole lauroxil) including 1019 adult patients with schizophrenia.

Patient Exposure

ARISTADA INITIO has been evaluated for safety in 170 adult patients in clinical trials in schizophrenia.

In pharmacokinetic studies, the safety profile of ARISTADA INITIO was generally consistent with that observed for ARISTADA.

ARISTADA (Aripiprazole Lauroxil) Trials in Adults with Schizophrenia

Commonly Observed Adverse Reactions with Aripiprazole Lauroxil

The most common adverse reaction (incidence ≥5% and at least twice the rate of placebo in patients treated with aripiprazole lauroxil) was akathisia.

Adverse Reactions Occurring at an Incidence of 2% or More in Aripiprazole Lauroxil-Treated Patients

Adverse reactions associated with the use of aripiprazole lauroxil (incidence of 2% or greater, rounded to the nearest percent and aripiprazole lauroxil incidence greater than placebo) that occurred were: injection site pain, increased weight, increased blood creatinine phosphokinase, akathisia, headache, insomnia, and restlessness.

Injection Site Reactions

ARISTADA INITIO

In pharmacokinetic studies evaluating ARISTADA INITIO, the incidences of injection site reactions with ARISTADA INITIO were similar to the incidence observed with aripiprazole lauroxil.

ARISTADA (Aripiprazole Lauroxil)

Injection site reactions were reported by 4% of patients treated with 441 mg aripiprazole lauroxil and 5% of patients treated with 882 mg aripiprazole lauroxil compared to 2% of patients treated with placebo. Most of these were injection site pain (3%, 4% and 2% in the 441 mg aripiprazole lauroxil, 882 mg aripiprazole lauroxil and placebo groups, respectively). Other injection site reactions (induration, swelling and redness) occurred at less than 1%.

Extrapyramidal Symptoms

In a schizophrenia efficacy study in aripiprazole lauroxil-treated patients, the incidence of other EPS-related events, excluding akathisia and restlessness, was 5% and 7% for patients on 441 mg and 882 mg, respectively, versus 4% for placebo-treated patients.

Dystonia

Symptoms of dystonia, prolonged abnormal contractions of muscle groups, may occur in susceptible individuals during the first few days of treatment. Dystonic symptoms include: spasm of the neck muscles, sometimes progressing to tightness of the throat, swallowing difficulty, difficulty breathing, and/or protrusion of the tongue. While these symptoms can occur at low doses, they occur more frequently and with greater severity with high potency and at higher doses of first generation antipsychotic drugs. An elevated risk of acute dystonia is observed in males and younger age groups.

Other Adverse Reactions Observed in Clinical Studies with Aripiprazole Lauroxil

The following listing does not include reactions: 1) already listed in previous tables or elsewhere in labeling, 2) for which a drug cause was remote, 3) which were so general as to be uninformative, 4) which were not considered to have significant clinical implications, or 5) which occurred at a rate equal to or less than placebo.

Cardiac – angina pectoris, tachycardia, palpitations

Gastrointestinal disorders – constipation, dry mouth

General disorders – asthenia

Musculoskeletal – muscular weakness

Nervous system disorders – dizziness

Psychiatric disorders – anxiety, suicide

Adverse Reactions Reported in Clinical Trials with Oral Aripiprazole

The following is a list of additional adverse reactions that have been reported in clinical trials with oral aripiprazole and not reported above for ARISTADA INITIO or aripiprazole lauroxil.

Blood and Lymphatic System Disorders: thrombocytopenia

Cardiac Disorders: bradycardia, atrial flutter, cardiorespiratory arrest, atrioventricular block, atrial fibrillation, myocardial ischemia, myocardial infarction, cardiopulmonary failure

Eye Disorders: photophobia, diplopia

Gastrointestinal Disorders: gastroesophageal reflux disease

General Disorders and Administration Site Conditions: peripheral edema, chest pain, face edema

Hepatobiliary Disorders: hepatitis, jaundice

Immune System Disorders: hypersensitivity

Injury, Poisoning, and Procedural Complications: fall, heat stroke

Investigations: blood prolactin decreased, weight decreased, hepatic enzyme increased, blood glucose increased, blood lactate dehydrogenase increased, gamma glutamyl transferase increased, blood prolactin increased, blood urea increased, blood creatinine increased, blood bilirubin increased, electrocardiogram QT prolonged, glycosylated hemoglobin increased

Metabolism and Nutrition Disorders: anorexia, hypokalemia, hyponatremia, hypoglycemia

Musculoskeletal and Connective Tissue Disorders: muscle tightness, rhabdomyolysis, mobility decreased

Nervous System Disorders: memory impairment, cogwheel rigidity, hypokinesia, bradykinesia, akinesia, myoclonus, coordination abnormal, speech disorder, choreoathetosis

Psychiatric Disorders: aggression, loss of libido, delirium, libido increased, anorgasmia, tic, homicidal ideation, catatonia, sleep walking

Renal and Urinary Disorders: urinary retention, nocturia

Reproductive System and Breast Disorders: erectile dysfunction, gynaecomastia, menstruation irregular, amenorrhea, breast pain, priapism

Respiratory, Thoracic, and Mediastinal Disorders: nasal congestion, dyspnea

Skin and Subcutaneous Tissue Disorders: rash, hyperhidrosis, pruritus, photosensitivity reaction, alopecia, urticaria

Vascular Disorders: hypotension, hypertension

6.2 Postmarketing Experience

The following adverse reactions have been identified during post-approval use of oral aripiprazole. Because these reactions are reported voluntarily from a population of uncertain size, it is not always possible to reliably estimate their frequency or to establish a causal relationship to drug exposure: occurrences of allergic reaction (anaphylactic reaction, angioedema, laryngospasm, pruritus/urticaria, or oropharyngeal spasm), pathological gambling, hiccups, blood glucose fluctuation, oculogyric crisis, drug reaction with eosinophilia and systemic symptoms (DRESS), and fecal incontinence.

7 DRUG INTERACTIONS

7.1 Drugs Having Clinically Important Interactions with ARISTADA INITIO

Table 4: Clinically Important Drug Interactions with ARISTADA INITIO
Strong CYP3A4 Inhibitors and CYP2D6 Inhibitors
Clinical Impact: | Concomitant use of oral aripiprazole with strong CYP3A4 or CYP2D6 inhibitors increased the exposure of aripiprazole compared to the use of oral aripiprazole alone [see Clinical Pharmacology (12.3)].
Intervention: | Avoid concomitant use of ARISTADA INITIO with strong CYP3A4 or strong CYP2D6 inhibitors because the dosage of ARISTADA INITIO cannot be modified [see Dosage and Administration (2.3)].
Examples: | itraconazole, clarithromycin, quinidine, fluoxetine, paroxetine
Strong CYP3A4 Inducers
Clinical Impact: | Concomitant use of oral aripiprazole and carbamazepine decreased the exposure of aripiprazole compared to the use of oral aripiprazole alone [see Clinical Pharmacology (12.3)].
Intervention: | Avoid concomitant use of ARISTADA INITIO with strong CYP3A4 inducers because the dosage of ARISTADA INITIO cannot be modified [see Dosage and Administration (2.3)].
Examples: | carbamazepine, rifampin
Antihypertensive Drugs
Clinical Impact: | Due to its alpha adrenergic antagonism, aripiprazole has the potential to enhance the effect of certain antihypertensive agents.
Intervention: | Avoid concomitant use of ARISTADA INITIO with antihypertensive drugs because the dosage of ARISTADA INITIO cannot be modified [see Warnings and Precautions (5.8)].
Examples: | carvedilol, lisinopril, prazosin
Benzodiazepines
Clinical Impact: | The intensity of sedation was greater with the combination of oral aripiprazole and lorazepam as compared to that observed with aripiprazole alone. The orthostatic hypotension observed was greater with the combination as compared to that observed with lorazepam alone [see Warnings and Precautions (5.8)].
Intervention: | Avoid concomitant use of ARISTADA INITIO with benzodiazepines because the dosage of ARISTADA INITIO cannot be modified [see Warnings and Precautions (5.8)].
Example: | lorazepam

7.2 Drugs Having No Clinically Important Interactions with ARISTADA INITIO

Based on pharmacokinetic studies with oral aripiprazole, no dosage adjustment of ARISTADA INITIO is required when administered concomitantly with famotidine, valproate, or lithium [see Clinical Pharmacology (12.3)].

In addition, no dosage adjustment is necessary for substrates of CYP2D6 (e.g., dextromethorphan, fluoxetine, paroxetine, or venlafaxine), CYP2C9 (e.g., warfarin), CYP2C19 (e.g., omeprazole, warfarin, escitalopram), or CYP3A4 (e.g., dextromethorphan) when co-administered with ARISTADA INITIO. Additionally, no dosage adjustment is necessary for valproate, lithium, lamotrigine, or sertraline when co-administered with ARISTADA INITIO [see Clinical Pharmacology (12.3)].

8 USE IN SPECIFIC POPULATIONS

8.1 Pregnancy

Pregnancy Exposure Registry

There is a pregnancy exposure registry that monitors pregnancy outcomes in women exposed to ARISTADA INITIO during pregnancy. For more information, contact the National Pregnancy Registry for Atypical Antipsychotics at 1-866-961-2388 or visit
http://womensmentalhealth.org/clinical-and-research-programs/pregnancyregistry/.

Risk Summary

Neonates exposed to antipsychotic drugs, including ARISTADA INITIO, during the third trimester of pregnancy are at risk for extrapyramidal and/or withdrawal symptoms following delivery (see Clinical Considerations). Overall available data from published epidemiologic studies of pregnant women exposed to aripiprazole have not established a drug-associated risk of major birth defects, miscarriage, or adverse maternal outcomes. There are risks to the mother associated with untreated schizophrenia and with exposure to antipsychotics, including ARISTADA INITIO, during pregnancy (see Clinical Considerations). Aripiprazole exposure during pregnancy may decrease milk supply in the post-partum period [see Use in Specific Populations (8.2)].

No teratogenicity was observed in animal reproductive studies with intramuscular administration of aripiprazole lauroxil to rats and rabbits during organogenesis at doses up to 8 and 23 times, respectively, the maximum recommended human dose (MRHD) of 675 mg based on body surface area (mg/m^2). However, aripiprazole caused developmental toxicity and possible teratogenic effects in rats and rabbits [see Data]. The background risk of major birth defects and miscarriage for the indicated population are unknown. In the U.S. general population, the estimated background risk of major birth defects and miscarriage in clinically recognized pregnancies is 2 to 4% and 15 to 20%, respectively. Advise pregnant women of the potential risk to a fetus.

Clinical Considerations

Disease-associated maternal and/or embryo/fetal risk

There is a risk to the mother from untreated schizophrenia, including increased risk of relapse, hospitalization, and suicide. Schizophrenia is associated with increased adverse perinatal outcomes, including preterm birth. It is not known if this is a direct result of the illness or other comorbid factors.

Fetal/Neonatal Adverse Reactions

Extrapyramidal and/or withdrawal symptoms, including agitation, hypertonia, hypotonia, tremor, somnolence, respiratory distress and feeding disorder have been reported in neonates who were exposed to antipsychotic drugs during the third trimester of pregnancy. These symptoms have varied in severity. Monitor neonates for extrapyramidal and/or withdrawal symptoms and manage symptoms appropriately. Some neonates recover within hours or days without specific treatment; others required prolonged hospitalization.

Data

Animal Data for ARISTADA (Aripiprazole Lauroxil)

Aripiprazole lauroxil did not cause adverse developmental or maternal effects in rats or rabbits when administered intramuscularly during the period of organogenesis at doses of 18, 49, or 144 mg/animal in pregnant rats which are approximately 1 to 8 times the MRHD of 675 mg based on mg/m^2, and at doses of 241, 723, and 2893 mg/animal in pregnant rabbits which are approximately 2 to 23 times the MRHD based on mg/m^2. However, aripiprazole caused developmental toxicity and possible teratogenic effects in rats and rabbits [see Data below].

Animal Data for Aripiprazole

Pregnant rats were treated with oral doses of 3, 10, and 30 mg/kg/day which are approximately 1 to 10 times the oral MRHD of 30 mg/day based on mg/m^2 of aripiprazole during the period of organogenesis. Treatment at the highest dose caused a slight prolongation of gestation and delay in fetal development, as evidenced by decreased fetal weight, and undescended testes. Delayed skeletal ossification was observed at 3 and 10 times the oral MRHD based on mg/m^2.

At 3 and 10 times the oral MRHD based on mg/m^2, delivered offspring had decreased body weights. Increased incidences of hepatodiaphragmatic nodules and diaphragmatic hernia were observed in offspring from the highest dose group (the other dose groups were not examined for these findings). A low incidence of diaphragmatic hernia was also seen in the fetuses exposed to the highest dose. Postnatally, delayed vaginal opening was seen at 3 and 10 times the oral MRHD based on mg/m^2 and impaired reproductive performance (decreased fertility rate, corpora lutea, implants, live fetuses, and increased post-implantation loss, likely mediated through effects on female offspring) along with some maternal toxicity were seen at the highest dose; however, there was no evidence to suggest that these developmental effects were secondary to maternal toxicity.

In pregnant rabbits treated with oral doses of 10, 30, and 100 mg/kg/day which are 2 to 11 times human exposure at the oral MRHD based on AUC and 6 to 65 times the oral MRHD based on mg/m^2 of aripiprazole during the period of organogenesis decreased maternal food consumption and increased abortions were seen at the highest dose as well as increased fetal mortality. Decreased fetal weight and increased incidence of fused sternebrae were observed at 3 and 11 times the oral MRHD based on AUC.

In rats treated with oral doses of 3, 10, and 30 mg/kg/day which are 1 to 10 times the oral MRHD based on mg/m^2 of aripiprazole perinatally and postnatally (from day 17 of gestation through day 21 postpartum), slight maternal toxicity and slightly prolonged gestation were seen at the highest dose. An increase in stillbirths and decreases in pup weight (persisting into adulthood) and survival were also seen at this dose.

8.2 Lactation

Risk Summary

Aripiprazole is present in human breast milk. Based on published case reports and pharmacovigilance reports, aripiprazole exposure during pregnancy and/or the postpartum period may lead to clinically relevant decreases in milk supply which may be reversible with discontinuation of the drug. There are also reports of aripiprazole exposure during pregnancy and no maternal milk supply in the post-partum period. Effects on milk supply may be mediated through decreases in prolactin levels, which have been observed [see Adverse Reactions (6.1)]. Monitor the breastfeed infant for dehydration and lack of appropriate weight gain. The development and health benefits of breastfeeding should be considered along with the mother's clinical need for ARISTADA INITIO and any potential adverse effects on the breastfed infant from ARISTADA INITIO or from the underlying maternal condition.

8.4 Pediatric Use

Safety and effectiveness of ARISTADA INITIO in pediatric patients have not been established.

8.5 Geriatric Use

Safety and effectiveness of ARISTADA INITIO in patients >65 years of age have not been evaluated.

Elderly patients with dementia-related psychosis treated with antipsychotic drugs are at an increased risk of death. ARISTADA INITIO is not approved for the treatment of patients with dementia-related psychosis [see Warnings and Precautions (5.1, 5.2)].

8.6 CYP2D6 Poor Metabolizers

Approximately 8% of Caucasians and 3-8% of Black/African Americans cannot metabolize CYP2D6 substrates and are classified as poor metabolizers (PM). Avoid use of ARISTADA INITIO in these patients because dosage adjustments are not possible (it is only available in one strength in a single-dose pre-filled syringe) [see Dosage and Administration (2.3), Clinical Pharmacology (12.3)].

8.7 Hepatic and Renal Impairment

No dosage adjustment for ARISTADA INITIO is required based on a patient's hepatic function (mild to severe hepatic impairment, Child-Pugh score between 5 and 15), or renal function (mild to severe renal impairment, glomerular filtration rate between 15 and 90 mL/minute) [see Clinical Pharmacology (12.3)].

8.8 Other Specific Populations

No dosage adjustment for ARISTADA INITIO is required on the basis of a patient's sex, race, or smoking status [see Clinical Pharmacology (12.3)].

10 OVERDOSAGE

10.1 Human Experience

Common adverse reactions (reported in at least 5% of all overdose cases) reported with oral aripiprazole overdosage (alone or in combination with other substances) include vomiting, somnolence, and tremor. Other clinically important signs and symptoms observed in one or more patients with aripiprazole overdoses (alone or with other substances) include acidosis, aggression, aspartate aminotransferase increased, atrial fibrillation, bradycardia, coma, confusional state, convulsion, blood creatine phosphokinase increased, depressed level of consciousness, hypertension, hypokalemia, hypotension, lethargy, loss of consciousness, QRS complex prolonged, QT prolonged, pneumonia aspiration, respiratory arrest, status epilepticus, and tachycardia.

10.2 Management of Overdosage

In case of overdosage, call the Poison control center immediately at 1-800-222-1222.

11 DESCRIPTION

ARISTADA INITIO contains aripiprazole lauroxil, an atypical antipsychotic.

The chemical name of aripiprazole lauroxil is 7-{4-[4-(2,3-dichlorophenyl)-piperazin-1-yl]butoxy}-2-oxo-3,4-dihydro-2H-quinolin-1-yl)methyl dodecanoate. The empirical formula is C36H51Cl2N3O4 and its molecular weight is 660.7 g/mol. The chemical structure is:

ARISTADA INITIO is available as a white to off-white sterile aqueous extended-release injectable suspension for intramuscular injection in the following strength of aripiprazole lauroxil (and deliverable volume from a single-dose pre-filled syringe): 675 mg (2.4 mL). This product's specific extended-release and dosing characteristics are derived from aripiprazole lauroxil's submicron particle size distribution. The inactive ingredients include polysorbate 20 (16.2 mg/mL), sodium chloride (3.3 mg/mL), sodium citrate dihydrate (8.1 mg/mL), sodium phosphate dibasic anhydrous (0.74 mg/mL), sodium phosphate monobasic dihydrate (0.84 mg/mL) and water for injection.

12 CLINICAL PHARMACOLOGY

12.1 Mechanism of Action

Aripiprazole lauroxil is a prodrug of aripiprazole. Following intramuscular injection, aripiprazole lauroxil is likely converted by enzyme-mediated hydrolysis to N-hydroxymethyl aripiprazole, which is then hydrolyzed to aripiprazole. The mechanism of action of aripiprazole in schizophrenia is unclear. However, efficacy could be mediated through a combination of partial agonist activity at dopamine D2 and serotonin 5-HT1A receptors and antagonist activity at 5-HT2A receptors.

12.2 Pharmacodynamics

Aripiprazole exhibits high affinity for dopamine D2 and D3 (Kis 0.34 and 0.8 nM respectively), serotonin 5-HT1A and 5-HT2A receptors (Kis 1.7 and 3.4 nM respectively), moderate affinity for dopamine D4, serotonin 5-HT2C and 5-HT7, alpha1-adrenergic and histamine H1 receptors (Kis 44 nM, 15 nM, 39 nM, 57 nM, and 61 nM, respectively), and moderate affinity for the serotonin reuptake site (Ki 98 nM). Aripiprazole has no appreciable affinity for cholinergic muscarinic receptors (IC50 > 1000 nM). Actions at receptors other than D2, 5-HT1A, and 5-HT2A could explain some of the adverse reactions of aripiprazole (e.g., the orthostatic hypotension observed with aripiprazole may be explained by its antagonist activity at adrenergic alpha1 receptors).

12.3 Pharmacokinetics

ARISTADA INITIO is a prodrug of aripiprazole and its activity is primarily due to aripiprazole, and to a lesser extent dehydro-aripiprazole (major metabolite of aripiprazole), which has been shown to have affinities for D2 receptors similar to aripiprazole and represents 30-40% of the aripiprazole exposure in plasma.

ARISTADA INITIO and ARISTADA are not interchangeable because of differing pharmacokinetic profiles. ARISTADA INITIO, 30 mg oral aripiprazole, and ARISTADA contribute to systemic aripiprazole exposure at different times throughout treatment initiation.

A pharmacokinetic (PK) bridging study demonstrated that an intramuscular injection of ARISTADA, a 30 mg dose of oral aripiprazole, and a single 675 mg dose of ARISTADA INITIO resulted in aripiprazole concentrations comparable to ARISTADA treatment initiated with 21 days of oral aripiprazole. A single strength of ARISTADA INITIO (i.e., 675 mg) was adequate for all dose levels of oral aripiprazole and ARISTADA.

Absorption

After single intramuscular injection of ARISTADA INITIO, the appearance of aripiprazole in the systemic circulation occurs on the day of injection; the median time to reach peak plasma exposures is approximately 27 days (range: 16 to 35 days).

With the addition of a single intramuscular injection of ARISTADA INITIO and 30 mg oral aripiprazole at the time of the first ARISTADA dose, aripiprazole concentrations reach relevant levels within 4 days.

Aripiprazole exposure was similar for deltoid and gluteal intramuscular injections of ARISTADA INITIO.

Distribution

Based on population pharmacokinetic analysis, the apparent volume of distribution of aripiprazole following intramuscular injection of ARISTADA was 268 L, indicating extensive extravascular distribution following absorption. Aripiprazole and its major metabolite are greater than 99% bound to serum proteins, primarily to albumin. In healthy human volunteers administered 0.5 mg/day to 30 mg/day oral aripiprazole for 14 days, there was dose-dependent D2 receptor occupancy indicating brain penetration of aripiprazole in humans.

Elimination

Metabolism

The biotransformation of ARISTADA INITIO likely involves enzyme-mediated hydrolysis to form N-hydroxymethyl-aripiprazole, which subsequently undergoes hydrolysis to aripiprazole. Elimination of aripiprazole is mainly through hepatic metabolism involving CYP3A4 and CYP2D6 [see Dosage and Administration (2.3)].

Excretion

For ARISTADA INITIO, the mean aripiprazole terminal elimination half-life was 15-18 days after injection. The significantly longer aripiprazole apparent half-life compared to oral aripiprazole (mean 75 hours) is attributed to the dissolution and formation rate-limited elimination of aripiprazole following ARISTADA INITIO administration.

Drug Interaction Studies

No specific drug interaction studies have been performed with ARISTADA INITIO. The drug interaction data provided below is obtained from studies with oral aripiprazole.

Effects of other drugs on the exposures of aripiprazole and dehydro-aripiprazole are summarized in Figure 1 and Figure 2, respectively. Based on simulation, a 4.5-fold increase in mean Cmax and AUC values at steady-state is expected when extensive metabolizers of CYP2D6 are administered with both strong CYP2D6 and CYP3A4 inhibitors. After oral administration, a 3-fold increase in mean Cmax and AUC values at steady-state is expected in poor metabolizers of CYP2D6 administered with strong CYP3A4 inhibitors.

Figure 1: The Effects of Other Drugs on Aripiprazole Pharmacokinetics

Figure 2: The Effects of Other Drugs on Dehydro-aripiprazole Pharmacokinetics

The effects of aripiprazole on the exposures of other drugs are summarized in Figure 3.

Figure 3: The Effects of Oral Aripiprazole on Pharmacokinetics of Other Drugs

Specific Populations

A population pharmacokinetic analysis showed no effect of sex, race or smoking on ARISTADA INITIO pharmacokinetics [see Use in Specific Populations (8.8)].

Exposures of aripiprazole and dehydro-aripiprazole using oral aripiprazole in specific populations are summarized in Figure 4 and Figure 5, respectively.

Figure 4: Effects of Intrinsic Factors on Aripiprazole Pharmacokinetics

Figure 5: Effects of Intrinsic Factors on Dehydro-aripiprazole Pharmacokinetics

13 NONCLINICAL TOXICOLOGY

13.1 Carcinogenesis, Mutagenesis, Impairment of Fertility

Carcinogenesis

Lifetime carcinogenicity studies have not been conducted with aripiprazole lauroxil.

Lifetime carcinogenicity studies with oral aripiprazole have been conducted in ICR mice and in Sprague-Dawley (SD) and F344 rats. Aripiprazole was administered for 2 years in the diet at doses of 1, 3, 10, and 30 mg/kg/day to ICR mice and 1, 3, and 10 mg/kg/day to F344 rats (0.2 to 5 times and 0.3 to 3 times the oral MRHD of 30 mg/day based on body surface area (mg/m^2), respectively). In addition, SD rats were dosed orally for 2 years at 10, 20, 40, and 60 mg/kg/day (3 to 19 times the oral MRHD based on mg/m^2). Aripiprazole did not induce tumors in male mice or rats. In female mice, the incidences of pituitary gland adenomas and mammary gland adenocarcinomas and adenoacanthomas were increased at dietary doses which are 0.1 to 0.9 times human exposure at the oral MRHD based on AUC and 0.5 to 5 times the oral MRHD on mg/m^2 basis. In female rats, the incidence of mammary gland fibroadenomas was increased at a dietary dose which is 0.1 times human exposure at the oral MRHD based on AUC and 3 times the oral MRHD on mg/m^2 basis; and the incidences of adrenocortical carcinomas and combined adrenocortical adenomas/carcinomas were increased at an oral dose which is 14 times human exposure at oral MRHD based on AUC and 19 times the oral MRHD on mg/m^2 basis.

Proliferative changes in the pituitary and mammary gland of rodents have been observed following chronic administration of other antipsychotic agents and are considered prolactin-mediated. The relevance for human risk of the findings of prolactin-mediated endocrine tumors in rodents is unknown.

Mutagenesis

Aripiprazole lauroxil was not mutagenic in the in vitro bacterial reverse mutation assay or clastogenic in the in vitro chromosome aberration assay in human peripheral blood lymphocytes.

Aripiprazole and its metabolite (2,3-DCPP) were clastogenic in the in vitro chromosome aberration assay in Chinese hamster lung (CHL) cells both in the presence and absence of metabolic activation. The metabolite, 2,3-DCPP, produced increases in numerical aberrations in the in vitro assay in CHL cells in the absence of metabolic activation. A positive response was obtained in the oral in vivo micronucleus assay in mice; however, the response was due to a mechanism not considered relevant to humans.

Impairment of Fertility

Animal Data for ARISTADA (Aripiprazole Lauroxil)

In a rat fertility study, aripiprazole lauroxil was administered intramuscularly. Males were treated with doses of 18, 49, or 144 mg/animal, which are approximately 0.6 to 5 times the MRHD of 675 mg on mg/m^2 basis, on Days 1, 21, and 42 prior to and through mating; females were treated at these doses, which are approximately 0.9 to 8 times the MRHD on mg/m^2 basis, once 14 days prior to mating.

In females, persistent diestrus was observed at all doses and the mean number of cycles was significantly decreased at the highest dose together with an increase in the copulatory interval (delay in mating). Additional changes at the high dose included slight increases in corpora lutea and pre-implantation loss, decline in mating, fertility, and fecundity indices in females and lower mating and fertility indices in males.

Animal Data for Aripiprazole

Female rats were treated with oral aripiprazole doses of 2, 6, and 20 mg/kg/day, which are 0.6 to 6 times the oral MRHD of 30 mg/day on mg/m^2 basis, from 2 weeks prior to mating through day 7 of gestation. Estrous cycle irregularities and increased corpora lutea were seen at all doses, but no impairment of fertility was observed. Increased pre-implantation loss was found at 2 and 6 times the oral MRHD on mg/m^2 basis and decreased fetal weight was noted at the highest dose which is 6 times the oral MRHD on mg/m^2 basis.

Male rats were treated with oral aripiprazole doses of 20, 40, and 60 mg/kg/day, which are 6 to 19 times the oral MRHD on mg/m^2 basis, from 9 weeks prior to and through mating. Disturbances in spermatogenesis at the highest dose and prostate atrophy at the mid and high doses were noted which are 13 and 19 times the oral MRHD on mg/m^2 basis, but no impairment of fertility was observed.

13.2 Animal Toxicology and/or Pharmacology

Animal Data for ARISTADA INITIO (Aripiprazole Lauroxil)

Intramuscular administration of aripiprazole lauroxil to rats and dogs was associated with injection site tissue reactions at all doses in rats treated up to 4 weeks at doses of 15, 29, and 103 mg/animal (which are approximately 0.6 to 4 times and 0.9 to 6 times the MRHD of 675 mg on mg/m^2 basis in males and females, respectively) and in dogs treated up to 4 weeks at doses of 147, 662, and 2058 mg/animal (which are approximately 0.7 to 10 times and 1 to 14 times the MRHD in males and females, respectively on mg/m^2 basis). These injection site tissue reactions consisted of localized granulomatous inflammation, granuloma formation, and/or subacute/chronic inflammation. Swelling occurred in both species, and transiently impaired limb function was observed in dogs. The granulomas did not completely resolve 2 months following the last injection in the 4-week studies in rats or dogs.

Orally administered aripiprazole produced retinal degeneration in albino rats in a 26-week chronic toxicity study at a dose of 60 mg/kg, which is 19 times the oral MRHD of 30 mg/day on mg/m^2 basis, and in a 2-year carcinogenicity study at doses of 40 mg/kg and 60 mg/kg, which are 13 and 19 times the oral MRHD on mg/m^2 basis and 7 to 14 times human exposure at the oral MRHD based on AUC. Evaluation of the retinas of albino mice and of monkeys did not reveal evidence of retinal degeneration. Additional studies to further evaluate the mechanism have not been performed. The relevance of this finding to human risk is unknown.

14 CLINICAL STUDIES

The effectiveness of ARISTADA INITIO, in combination with oral aripiprazole, for initiation of ARISTADA when used for the treatment of schizophrenia in adults was established by adequate and well-controlled studies of oral aripiprazole and ARISTADA in adult patients with schizophrenia [see ARISTADA prescribing information] and a single PK bridging study [see Clinical Pharmacology (12.3)].

16 HOW SUPPLIED/ STORAGE AND HANDLING

16.1 How Supplied

ARISTADA INITIO extended-release injectable suspension is available in a strength of 675 mg in 2.4 mL. The kit contains a 5-mL pre-filled syringe containing ARISTADA INITIO as a sterile white to off-white aqueous extended-release injectable suspension with safety needles.

- A 675 mg strength kit (NDC 65757-500-03; gray label) contains three safety needles; a 1-inch (25 mm) 21 gauge, a 1½-inch (38 mm) 20 gauge, and a 2-inch (50 mm) 20 gauge needle.

16.2 Storage

Store at room temperature 20°C to 25°C (68°F to 77°F) with excursions permitted between 15°C and 30°C (between 59°F and 86°F). Do not freeze.

17 PATIENT COUNSELING INFORMATION

Advise patients to read FDA-approved patient labeling (Medication Guide).

Neuroleptic Malignant Syndrome

Counsel patients about a potentially fatal adverse reaction referred to as NMS that has been reported in association with administration of antipsychotic drugs. Advise patients to contact a healthcare provider or report to the emergency room if they experience signs or symptoms of NMS [see Warnings and Precautions (5.4)].

Tardive Dyskinesia

Advise patients that abnormal involuntary movements have been associated with administration of antipsychotic drugs. Counsel patients to notify their healthcare provider if they notice any movements which they cannot control in their face, tongue, or other body part [see Warnings and Precautions (5.5)].

Metabolic Changes (Hyperglycemia and Diabetes Mellitus, Dyslipidemia, and Weight Gain)

Educate patients about the risk of metabolic changes, how to recognize symptoms of hyperglycemia and diabetes mellitus, and the need for specific monitoring, including blood glucose, lipids, and weight [see Warnings and Precautions (5.6)].

Pathological Gambling and Other Compulsive Behaviors

Advise patients and their caregivers of the possibility that they may experience compulsive urges to shop, intense urges to gamble, compulsive sexual urges, binge eating and/or other compulsive urges and the inability to control these urges. In some cases, but not all, the urges were reported to have stopped when the dose was reduced or stopped [see Warnings and Precautions (5.7)].

Orthostatic Hypotension

Educate patients about the risk of orthostatic hypotension (symptoms include feeling dizzy or lightheaded upon standing), particularly at the time of initiating treatment, or re-initiating treatment [see Warnings and Precautions (5.8)].

Falls

Advise patients and their caregivers of the possibility that they may experience somnolence, postural hypotension, or motor and sensory instability, which may lead to the risk of falls, particularly in patients with diseases, conditions, or medications that could exacerbate these effects [see Warnings and Precautions (5.9)].

Leukopenia, Neutropenia and Agranulocytosis

Advise patients with a pre-existing low WBC count or a history of drug-induced leucopenia/neutropenia that they should have their CBC monitored [see Warnings and Precautions (5.10)].

Interference with Cognitive and Motor Performance

Because ARISTADA INITIO may have the potential to impair judgment, thinking or motor skills, instruct patients to be cautious about operating hazardous machinery, including automobiles, until they are reasonably certain that therapy does not affect them adversely [see Warnings and Precautions (5.12)].

Heat Exposure and Dehydration

Advise patients regarding appropriate care in avoiding overheating and dehydration [see Warnings and Precautions (5.13)].

Concomitant Medication

Advise patients to inform their physicians if they are taking, or plan to take, any prescription or over-the-counter drugs, since there is a potential for interactions [see Drug Interactions (7)].

Pregnancy

Advise patients to notify their healthcare provider if they become pregnant or intend to become pregnant during treatment with ARISTADA INITIO. Advise patients that ARISTADA INITIO may cause extrapyramidal and/or withdrawal symptoms (agitation, hypertonia, hypotonia, tremor, somnolence, respiratory distress, and feeding disorder) in a neonate. Advise patients that there is a pregnancy registry that monitors pregnancy outcomes in women exposed to ARISTADA INITIO during pregnancy [see Use in Specific Populations (8.1)].

Lactation

ARISTADA INITIO use during pregnancy may affect milk supply. Advise the lactating patient to discuss any plans for breastfeeding with a healthcare provider, and to monitor the breastfed infant for dehydration and lack of appropriate weight gain [see Use in Specific Populations (8.2)].

For additional information, visit www.ARISTADA.com or call 1-866-274-7823

Manufactured and marketed by:
Alkermes, Inc.
Waltham, MA 02451

Alkermes

©2025 Alkermes, Inc. All rights reserved.

ALKERMES® is a registered trademark of Alkermes, Inc., ARISTADA INITIO® is a registered trademark used by Alkermes, Inc. under license and ARISTADA® is a registered trademark used by Alkermes, Inc. under license.

Printed in U.S.A.

MEDICATION GUIDE
ARISTADA INITIO® (air-is-TAH-dah i-ni'-she-oh)
(aripiprazole lauroxil)
extended-release injectable suspension, for intramuscular use

What is the most important information I should know about ARISTADA INITIO?
ARISTADA INITIO may cause serious side effects, including:

- Increased risk of death in elderly people with dementia-related psychosis. ARISTADA INITIO increases the risk of death in elderly people who have lost touch with reality (psychosis) due to confusion and memory loss (dementia). ARISTADA INITIO is not for the treatment of people with dementia-related psychosis.

What is ARISTADA INITIO?
ARISTADA INITIO is a prescription medicine given as a one-time injection and is used in combination with oral aripiprazole to start ARISTADA treatment, or re-start ARISTADA treatment after a missed dose, when ARISTADA is used for the treatment of schizophrenia in adults.
It is not known if ARISTADA INITIO is safe and effective in children.

Do not receive ARISTADA INITIO if you are allergic to aripiprazole or any of the ingredients in ARISTADA INITIO. See the end of this Medication Guide for a complete list of ingredients in ARISTADA INITIO.

Before you receive ARISTADA INITIO, tell your healthcare provider about all of your medical conditions, including if you:

- have not taken ABILIFY®, ABILIFY MAINTENA® or any aripiprazole product before
- have or had heart problems or a stroke
- have diabetes or high blood sugar or a family history of diabetes or high blood sugar. Your healthcare provider should check your blood sugar before you receive ARISTADA INITIO.
- have or had low or high blood pressure
- have or had seizures (convulsions)
- have or had a low white blood cell count
- are pregnant or plan to become pregnant. It is not known if ARISTADA INITIO will harm your unborn baby.
  - If you become pregnant after you receive ARISTADA INITIO, talk to your healthcare provider about registering with the National Pregnancy Registry for Atypical Antipsychotics. You can register by calling 1-866-961-2388 or visit http://womensmentalhealth.org/clinical-and-research-programs/pregnancyregistry/
- are breastfeeding or plan to breastfeed. ARISTADA INITIO can pass into your breast milk and it is not known if it may harm your baby. Talk to your healthcare provider about the best way to feed your baby after you receive ARISTADA INITIO.

Tell your healthcare provider about all the medicines you take, including prescription and over-the-counter medicines, vitamins, and herbal supplements.
ARISTADA INITIO and other medicines may affect each other causing possible serious side effects. ARISTADA INITIO may affect the way other medicines work, and other medicines may affect how ARISTADA INITIO works.
Your healthcare provider can tell you if it is safe to receive ARISTADA INITIO with your other medicines. Do not start or stop any medicines after you receive ARISTADA INITIO without talking to your healthcare provider first.

How will I receive ARISTADA INITIO?

- Follow your ARISTADA INITIO treatment schedule exactly as your healthcare provider tells you to.
- ARISTADA INITIO is a one-time injection given by your healthcare provider, into the muscle (intramuscular) of your arm or buttock.
- ARISTADA INITIO is given in combination with a single dose of oral aripiprazole. You may also receive your first injection of ARISTADA on the same day you receive ARISTADA INITIO or up to 10 days after you receive ARISTADA INITIO.
- ARISTADA INITIO should only be used as a one-time dose to start ARISTADA treatment or to re-start ARISTADA treatment after a missed dose. ARISTADA INITIO is not meant for repeated dosing.

What should I avoid after I receive ARISTADA INITIO?

- Do not drive a car, operate hazardous machinery, or do other dangerous activities until you know how ARISTADA INITIO affects you. ARISTADA INITIO may affect your judgment, thinking or motor skills.
- Avoid becoming too hot or dehydrated.
  - Do not exercise too much.
  - In hot weather, stay inside in a cool place if possible.
  - Stay out of the sun.
  - Do not wear too much clothing or heavy clothing.
  - Drink plenty of water.

What are the possible side effects of ARISTADA INITIO?
ARISTADA INITIO may cause serious side effects, including:

- See “What is the most important information I should know about ARISTADA INITIO?”
- Cerebrovascular problems (including stroke) in elderly people with dementia-related psychosis that can lead to death.
- Neuroleptic malignant syndrome (NMS), a serious condition that can lead to death. Call your healthcare provider or go to the nearest hospital emergency room right away if you have some or all of the following signs and symptoms of NMS:
  - high fever
  - stiff muscles
  - confusion
  - sweating
  - changes in pulse, heart rate, and blood pressure

- Uncontrolled body movements (tardive dyskinesia). ARISTADA INITIO may cause movements that you cannot control in your face, tongue, or other body parts. Tardive dyskinesia may not go away.
- Problems with your metabolism such as:
  - high blood sugar (hyperglycemia). Increases in blood sugar can happen in some people who receive ARISTADA INITIO. Extremely high blood sugar can lead to coma or death. If you have diabetes or risk factors for diabetes (such as being overweight or a family history of diabetes), your healthcare provider should check your blood sugar before you receive ARISTADA INITIO.
    Call your healthcare provider if you have any of these symptoms of high blood sugar:
    - feel very thirsty
    - feel very hungry
    - feel sick to your stomach
    - need to urinate more than usual
    - feel weak or tired
    - feel confused, or your breath smells fruity

- increased fat levels (cholesterol and triglycerides) in your blood.
- weight gain.

- Unusual and uncontrollable (compulsive) urges. Some people taking aripiprazole have had strong unusual urges to gamble and gambling that cannot be controlled (compulsive gambling). Other compulsive urges include sexual urges, shopping, and eating or binge eating. If you or your family members notice that you are having unusual strong urges, talk to your healthcare provider.
- Decreased blood pressure (orthostatic hypotension). You may feel lightheaded or faint when you rise too quickly from a sitting or lying position.
- Falls. ARISTADA INITIO may make you sleepy or dizzy, may cause a decrease in your blood pressure when changing position and can slow your thinking and motor skills which may lead to falls that can cause fractures or other injuries.
- Low white blood cell count
- Seizures (convulsions)
- Problems controlling your body temperature. See “What should I avoid after I receive ARISTADA INITIO?”
- Difficulty swallowing

The most common side effects of ARISTADA INITIO include restlessness or feeling like you need to move (akathisia).
These are not all the possible side effects of ARISTADA INITIO.
Call your doctor for medical advice about side effects. You may report side effects to FDA at 1-800-FDA-1088.

General information about ARISTADA INITIO
If you would like more information, talk with your healthcare provider. You can ask your pharmacist or healthcare provider for information about ARISTADA INITIO that is written for health professionals.

What are the ingredients in ARISTADA INITIO?
Active ingredient: aripiprazole lauroxil
Inactive ingredients: polysorbate 20, sodium chloride, sodium citrate dihydrate, sodium phosphate dibasic anhydrous, sodium phosphate monobasic dihydrate and water for injection
Manufactured and marketed by: Alkermes, Inc., Waltham, MA 02451
For more information, go to www.ARISTADA.com or call 1-866-274-7823.

This Medication Guide has been approved by the U.S. Food and Drug Administration

Revised 12/2023

Principal Display Panel - Aristada Initio Carton Label

NDC: 65757-500-03

675 mg/2.4 mL

Rx only

Aristada Initio®

aripiprazole lauroxil

extended-release injectable suspension

Starter Dose

675 mg

STARTER
DOSE

- For initiation with any Aristada® dose
- Only use to initiate or re-initiate Aristada treatment
- NOT for repeated dosing

For gluteal or deltoid intramuscular injection only
Aristada Initio is NOT interchangeable with Aristada due to
differing pharmacokinetic profiles

Single-dose injection - Entire Content of Syringe Must
Be Administered by Healthcare Professional Only

OPEN HERE